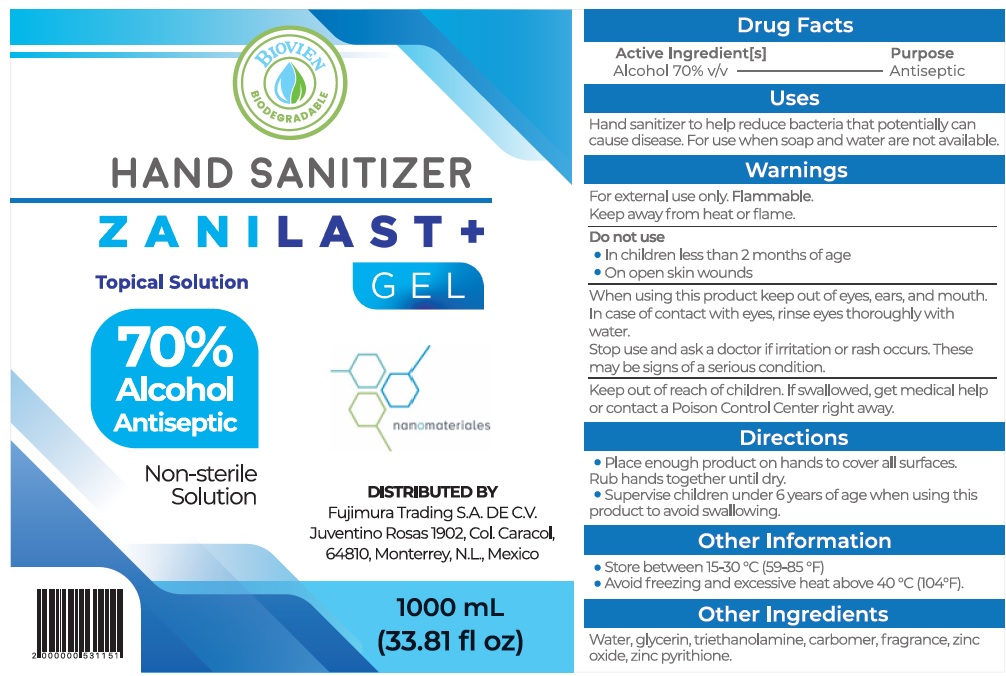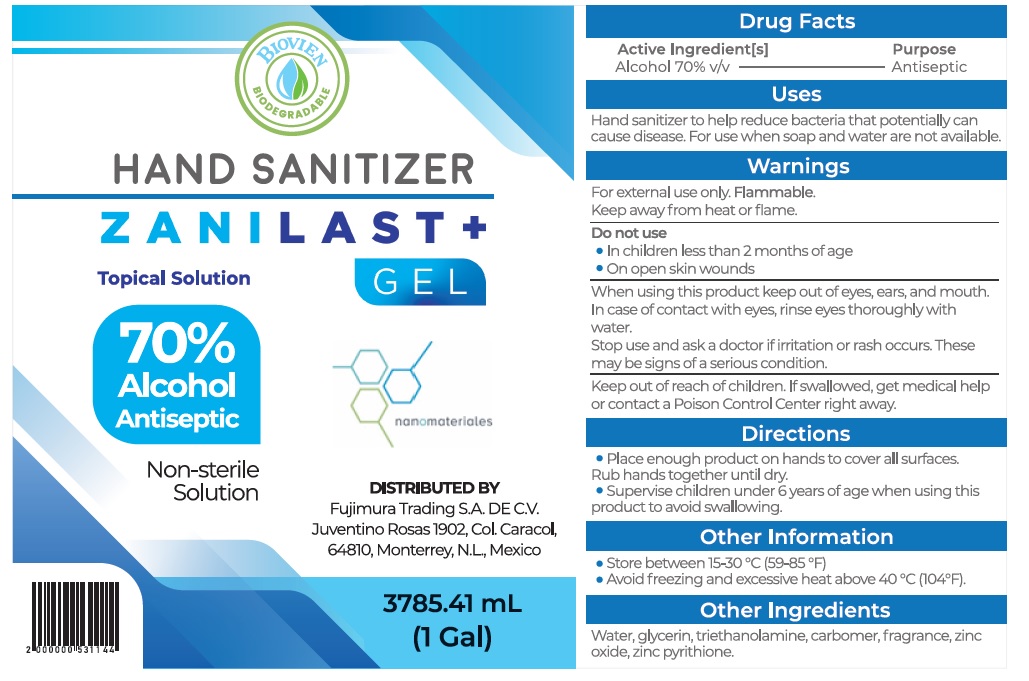 DRUG LABEL: ZANILAST Plus
NDC: 69912-008 | Form: GEL
Manufacturer: Nanomateriales, S.A. de C.V.
Category: otc | Type: HUMAN OTC DRUG LABEL
Date: 20200707

ACTIVE INGREDIENTS: ALCOHOL 0.7 mg/1 mL
INACTIVE INGREDIENTS: WATER; GLYCERIN; TROLAMINE; CARBOMER HOMOPOLYMER, UNSPECIFIED TYPE; ZINC OXIDE; PYRITHIONE ZINC

ZANILAST+ Gel

Active Ingredient[s]

Alcohol 70% v/v

Purpose

Antiseptic

Uses

Hand sanitizer to help reduce bacteria that potentially can cause disease. For use when soap and water are not available.

Warnings

For external use only. Flammable. Keep away from heat or flame.

Do not use

- In children less than 2 months of age
- On open skin wounds

When using this product

keep out of eyes,ears, and mouth. In case of contact with eyes,rinse eyes thoroughly with water.

Stop use and ask a doctor

if irritation or rash occurs. These may be signs of a serious condition.

Keep out of reach of children.

If swallowed, get medical help or contact a Poison Control Center right away.

Directions

- Place enough product on hands to cover all surfaces. Rub hands together until dry.
- Supervise children under 6 years of age when using this product to avoid swallowing.

Other Information

- Store between 15-30 °C (59-85 °F)
- Avoid freezing and excessive heat above 40 °C (104°F).

Other Ingredients

Water,glycerin, triethanolamine,carbomer,fragrance,zinc oxide,zinc pyrithione.